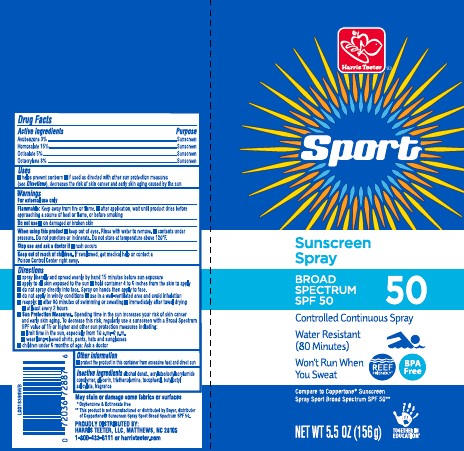 DRUG LABEL: sunscreen
NDC: 72036-938 | Form: SPRAY
Manufacturer: Harris Teeter
Category: otc | Type: HUMAN OTC DRUG LABEL
Date: 20260204

ACTIVE INGREDIENTS: HOMOSALATE 150 mg/1 g; OCTISALATE 50 mg/1 g; OCTOCRYLENE 80 mg/1 g; AVOBENZONE 30 mg/1 g
INACTIVE INGREDIENTS: ALCOHOL; STEAROXYTRIMETHYLSILANE; GLYCERIN; TROLAMINE; TOCOPHEROL; BUTYLOCTYL SALICYLATE

Harris Teeter 938.002/938AB
Sport Sunscreen Spray SPF 50

active ingredients

Avobenzone 3%

Homosalate 15%

Octisalate 5%

Octocrylene 8%

purpose

sunscreen

uses

■ helps prevent sunburn

■ if used as directed with other sun protection measures (see Directions), decreases the risk of skin cancer and early skin aging caused by the sun

warnings

For external use only

Flammable

Keep away from fire or flame.

- after application, wait until product dries before approaching a source of heat or flame, or before smoking

do not use

- on damaged or broken skin

When using this product

- keep out of eyes. Rinse with water to remove.
- contents under pressure. Do not puncture or incinerate. Do not store at temperature above 120ºF.

stop use and ask a doctor if

- rash occurs

Keep out of reach of children.

If swallowed, get medical help or contact a Poison Conrol Center right away.

direction

■ spray liberally and spread evenly by hand 15 minutes before sun exposure
■ apply to all skin exposed to the sun
■ hold container 4 to 6 inches from the skin to apply
■ do not spray directly into face. Spray on hands then apply to face.
■ do not apply in windy conditions
■ use in a well-ventilated area and avoid inhalation
■ reapply:
■ after 80 minutes of swimming or sweating
■ immediately after towel drying
■ at least every 2 hours
■ Sun Protection Measures. Spending time in the sun increases your risk of skin cancer and early skin aging. To decrease this risk, regularly use a sunscreen with a Broad Spectrum SPF value of 15 or higher and other sun protection measures including:
■ limit time in the sun, especially from 10 a.m.–2 p.m.
■ wear long-sleeved shirts, pants, hats and sunglasses
■ children under 6 months of age: Ask a doctor

other information

- protect the product in this container from excessive heat and direct sun

inactive ingredients

alcohol denat., acrylates/octylacrylamide copolymer, glycerin, triethanolamine, tocopherol, butyloctyl salicylate, fragrance

Claims

May stain or damage some fabrics of surfaces

*Oxybenzone & Octinoxate free

Disclaimer

**This product is not manufactured or distributed by Bayer, distributor of CoppertoneSunscreen Spray Sport Broad Spectrum SPF 50.

ADVERSE REACTION

PROUDLY DISTRIBUTED BY:

HARRIS TEETER, LLC, MATTHEWS, NC 28105

1-800-432-6111 or harristeeter.com

principal display panel

Harris Teeter™

Sport

Sunscreen Spray

BROAD SPECTRUM SPF 50

50

Controlled Continuous Spray

Water Resistant (80 Minutes)

Won't Run When You Sweat

REEF FRIENDLY*

BPA Free

Compare to Coppertone®Sunscreen Spray Sport Broad Spectrum SPF 50**

NET WT 5.5 OZ (156 g)

TOGETHER IN EDUCATION